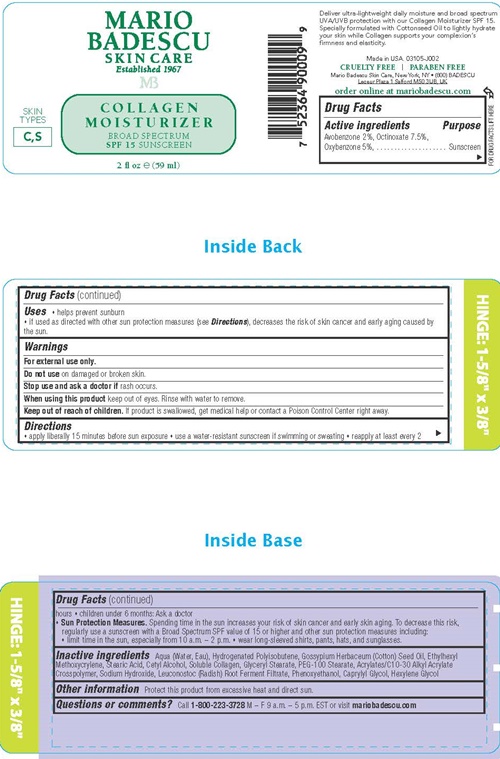 DRUG LABEL: Mario Badescu Collagen SPF 15
NDC: 54111-136 | Form: LOTION
Manufacturer: Bentley Laboratories LLC
Category: otc | Type: HUMAN OTC DRUG LABEL
Date: 20240910

ACTIVE INGREDIENTS: AVOBENZONE 1.2 g/59 mL; OCTINOXATE 4.24 g/59 mL; OXYBENZONE 2.84 g/59 mL
INACTIVE INGREDIENTS: WATER; HYDROGENATED POLYBUTENE (1300 MW); COTTONSEED OIL; ETHYLHEXYL METHOXYCRYLENE; STEARIC ACID; CETYL ALCOHOL; MARINE COLLAGEN, SOLUBLE; GLYCERYL MONOSTEARATE; PEG-100 STEARATE; CARBOMER INTERPOLYMER TYPE A (ALLYL SUCROSE CROSSLINKED); SODIUM HYDROXIDE; LEUCONOSTOC/RADISH ROOT FERMENT FILTRATE; PHENOXYETHANOL; CAPRYLYL GLYCOL; HEXYLENE GLYCOL

Mario Badescu Collagen Moisturizer SPF 15

Drug Facts Active ingredients

Avobenzone 2%
Octinoxate 7.5%
Oxybenzone 5%

Purpose

Sunscreen

Uses

- helps prevent sunburn
- If used as directed with other sun protection measures (see Directions), decreases the risk of skin cancer and early aging caused by the sun.

Warnings

For external use only.

Do not use on damaged or broken skin.

Stop use and ask a doctor if rash occurs.

When using this product keep out of eyes. Rinse with water to remove

Keep out of reach of children.

If product is swallowed, get medical help or contact a Poison Control Center right away.

Directions

- apply liberally 15 minutes before sun exposure
- use a water-resistant sunscreen if swimming or sweating
- reapply at least every 2 hours
- children under 6 months: Ask a doctor
- Sun Protection Measures. Spending time in the sun increases your risk of skin cancer and early aging. To decrease this risk, regularly use a sunscreen with a Broad Spectrum SPF value of 15 or higher and other sun protection measures including:
- limit time in the sun, especially from 10 a.m. - 2 p.m.
- wear long-sleeved shirts, pants, hats, and sunglasses.

Inactive ingredients

Aqua (Water, Eau), Hydrogenated Polysobutene, Gossyplum Herbaceum (Cotton) Seed Oil, Ethylhexyl Methoxycrylene, Stearic Acid, Cetyl Alcohol, Soluble Collagen, Glyceryl Stearate, PEG-100 stearate, Acrylates/C10-30 Acrylate Crosspolymer, Sodium Hydroxide, Leuconostoc (Radish) Root Ferment Filtrate, Phenoxyethanol, Caprylyl Glycol, Hexylene Glycol

Other information

Protect this product from excessive heat and direct sun.

Questions or comments?

Call 1-800-223-3728 M - F 9 a.m. - 5 p.m. EST or visit mariobadescu.com

Mario Badescu Collagen Moisturizer SPF 15 product label

MARIO
BADESCU
SKIN CARE
Established 1967
MB
COLLAGEN
MOISTURIZER
BROAD SPECTRUM
SPF 15 SUNSCREEN

SKIN
TYPES
C,S

2 fl oz (59 ml)

Deliver ultra-lightweight daily moisture and broad spectrum UVA/UVB protection with our Collagen Moisturizer SPF 15. Specially formulated with Cottonseed Oil to lightly hydrate your skin while Collagen supports your complexion's firmness and elasticity

Made in the USA. 03105-J002
CRUELTY FREE l PARABEN FREE
Mario Badescu Skin Care, New York, NY • (800) BADESCU
Leceur Plaza 1 Salford M50 3UB, UK

order online at mario badescu.com

res